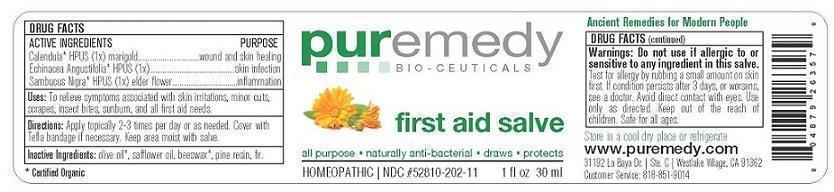 DRUG LABEL: FIRST AID
NDC: 52810-212 | Form: SALVE
Manufacturer: PUREMEDY
Category: homeopathic | Type: HUMAN OTC DRUG LABEL
Date: 20240111

ACTIVE INGREDIENTS: SAMBUCUS NIGRA FLOWER 1 [hp_X]/100 mL; CALENDULA OFFICINALIS FLOWER 1 [hp_X]/100 mL; ECHINACEA ANGUSTIFOLIA 1 [hp_X]/100 mL
INACTIVE INGREDIENTS: CANADA BALSAM; OLIVE OIL; SAFFLOWER OIL; YELLOW WAX; PINE NEEDLE OIL (PINUS SYLVESTRIS)

FIRST AID (52810-212)

- ACTIVE INGREDIENTS

ORGANIC SAMBUCUS NIGRA (1X) HPUS (ELDERBERRY)

ORGANIC CALENDULA OFFICINALIS (1X) HPUS (MARIGOLD)

ECHINACEA ANGUSTIFOLIA (1X) HPUS

PURPOSE

PROPERTIES

SKIN PROTECTANT

INDICATIONS AND USAGE

USES: TO RELIEVE SYMPTOMS ASSOCIATED WITH MINOR SKIN IRRITATIONS, BOILS, CUTS, BURNS, AND OTHER FIRST AID NEEDS.

DOSAGE AND ADMINISTRATION

DIRECTIONS: APPLY TO AFFECTED AREA 2-4 TIMES PER DAY OR AS NEEDED. COVER WITH A BANDAID OR TELFA BANDAGE IF NECESSARY. DO NOT DRESS WITH GAUZA.

INACTIVE INGREDIENT

OTHER INGREDIENTS: ORGANIC OLIVE OIL, SAFFLOWER OIL, ORGANIC BEESWAX.

WARNINGS

WARNING: TEST FOR ALLERGY BY RUBBING A SMALL AMOUNT ON SKIN FIRST. DO NOT USE IF ALLERGIC TO OR HYPER-SENSITIVE TO ANY INGREDIENT IN THIS SALVE. IF CONDITION PERSISTS OR WORSENS CONSULT YOUR HEALTH CARE PROVIDER.

KEEP OUT OF REACH OF CHILDREN.

QUESTIONS

CUSTOMER SERVICE 310-526-6108